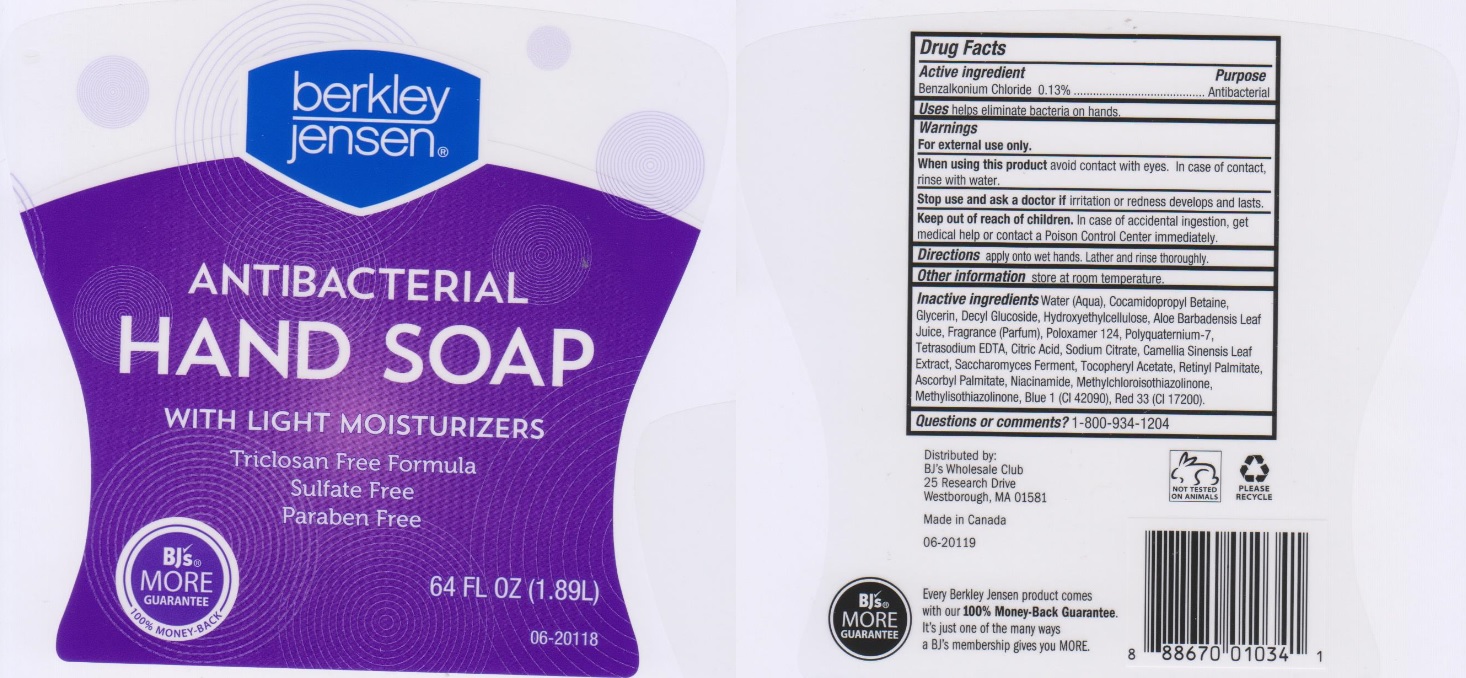 DRUG LABEL: Berkley Jenson Antibacterial Hand
NDC: 68391-151 | Form: LIQUID
Manufacturer: BJWC
Category: otc | Type: HUMAN OTC DRUG LABEL
Date: 20200317

ACTIVE INGREDIENTS: BENZALKONIUM CHLORIDE 1.3 mg/1 mL
INACTIVE INGREDIENTS: WATER; COCAMIDOPROPYL BETAINE; GLYCERIN; DECYL GLUCOSIDE; HYDROXYETHYL CELLULOSE (5000 CPS AT 1%); ALOE VERA LEAF; POLOXAMER 124; POLYQUATERNIUM-7 (70/30 ACRYLAMIDE/DADMAC; 1600000 MW); EDETATE SODIUM; CITRIC ACID MONOHYDRATE; SODIUM CITRATE; GREEN TEA LEAF; SACCHAROMYCES LYSATE; .ALPHA.-TOCOPHEROL ACETATE, DL-; VITAMIN A PALMITATE; ASCORBYL PALMITATE; NIACINAMIDE; METHYLCHLOROISOTHIAZOLINONE; METHYLISOTHIAZOLINONE; FD&C BLUE NO. 1; D&C RED NO. 33

Drug Facts

Active ingredient

Benzalkonium Chloride 0.13%

Purpose

Antibacterial

Uses

helps eliminate bacteria on hands.

Warnings

For external use only.

When using this product

avoid contact with eyes. In case of contact, rinse with water.

Stop use and ask a doctor if

irritation or redness develops and lasts

Keep out of reach of children.

In case of accidental ingestion, get medical help or contact a Poison Control Center immediately.

Directions

appy onto wet hands. Lather and rinse thoroughly

Other information

store at room temperature.

Inactive ingredients

Water (Aqua), Cocamidopropyl Betaine, Glycerin, Decyl Glucoside, Hydroxyethylcellulose, Aloe Barbadensis Leaf Juice, Fragrance (Parfum), Poloxamer 124, Polyquaternium-7, Tetrasodium EDTA, Citric Acid, Sodium Citrate, Camellia Sinensis Leaf Extract, Saccharomyces Ferment, Tocopheryl Acetate, Retinyl Palmitate, Ascorbyl Palmitate, Niacinamide, Methylchloroisothiazolinone, Methylisothiazolinone, Blue 1 (CI 42090), Red 33 (CI 17200).

Questions or comments?

1-800-934-1204